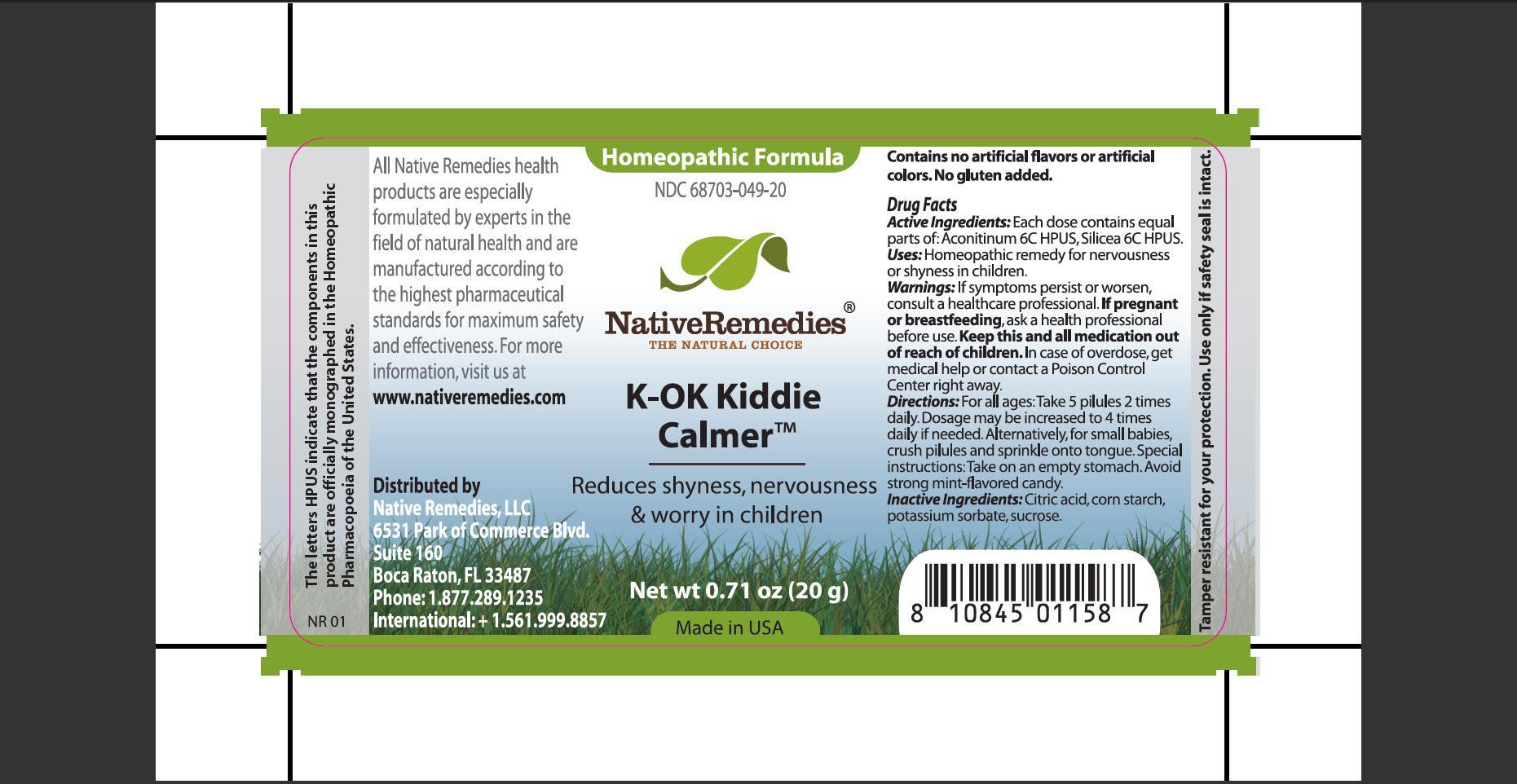 DRUG LABEL: K-OK Kiddie Calmer
NDC: 68703-049 | Form: GRANULE
Manufacturer: Native Remedies, LLC
Category: homeopathic | Type: HUMAN OTC DRUG LABEL
Date: 20120829

ACTIVE INGREDIENTS: ACONITUM NAPELLUS 6 [hp_C]/100 mg; SILICON DIOXIDE 6 [hp_C]/100 mg
INACTIVE INGREDIENTS: CITRIC ACID MONOHYDRATE; STARCH, CORN; POTASSIUM SORBATE; SUCROSE

K-OK Kiddie Calmer

PURPOSE

Reduces shyness, nervousness and worry in children.

ACTIVE INGREDIENT

Active Ingredients: Each dose contains equal parts of: Aconitinum 6C HPUS, Silicea 6C HPUS.

INDICATIONS AND USAGE

Uses: Homeopathic remedy for nervousness or shyness in children.

WARNINGS

Warnings: If symptoms persist or worsen, consult a healthcare professional.

PREGNANCY OR BREAST FEEDING

If pregnant or breastfeeding, ask a health professional before use.

KEEP OUT OF REACH OF CHILDREN

Keep this and all medication out of reach of children.

OVERDOSAGE

In case of overdose, get medical help or contact a Poison Control Center right away.

DOSAGE AND ADMINISTRATION

Directions: For all ages: Take 5 pilules 2 times daily. Dosage may be increased to 4 times daily if needed. Alternatively, for small babies, crush piulules and sprinkle onto tongue. Special instructions: Take on an empty stomach. Avoid strong mint-flavored candy.

INACTIVE INGREDIENT

Inactive Ingredients: Citric acid, corn starch, potassium sorbate, sucrose.

PATIENT COUNSELING INFORMATION

The letters HPUS indicate that the components in this product are officially monographed in the Homeopathic Pharmacopoeia of the United States.

All Native Remedies health products are especially formulated by experts in the field of natural health and are manufactured according to the highest pharmaceutical standards for maximum safety and effectiveness. For more information, visit us at www.nativeremedies.com

Distributed by
Native Remedies, LLC
6531 Park of Commerce Blvd.
Suite 160
Boca Raton, FL 33487
Phone: +1.877.289.1235
International: +1.561.999.8857

Contains no artificial flavors or artificial colors. No gluten added.

STORAGE AND HANDLING

Tamper resistant for your protection. Use only if safety seal is intact.